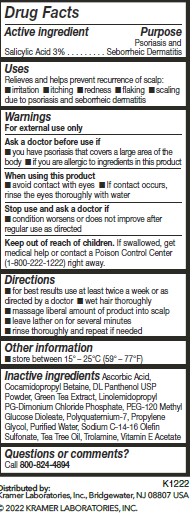 DRUG LABEL: Nizoral Psoriasis
NDC: 44038-0202 | Form: SHAMPOO
Manufacturer: Accupac LLC
Category: otc | Type: HUMAN OTC DRUG LABEL
Date: 20240918

ACTIVE INGREDIENTS: SALICYLIC ACID 3 g/100 mL
INACTIVE INGREDIENTS: TEA TREE OIL; .ALPHA.-TOCOPHEROL ACETATE; PANTHENOL; PEG-120 METHYL GLUCOSE DIOLEATE; GREEN TEA LEAF; POLYQUATERNIUM-7 (70/30 ACRYLAMIDE/DADMAC; 1600000 MW); WATER; SODIUM C14-16 OLEFIN SULFONATE; ASCORBIC ACID; COCAMIDOPROPYL BETAINE; LINOLEAMIDOPROPYL PROPYLENE GLYCOL-DIMONIUM CHLORIDE PHOSPHATE; PROPYLENE GLYCOL; TROLAMINE

Active ingredient

Salicylic Acid 3%

Purpose

Psoriasis and Seborreic Dermatitis

Uses

Relieves and helps prevent recurrence of scalp:

irritation

itching

redness

flaking

scaling due to psoriasis and seborreic dermatitis

WARNINGS

Ask a doctor before use if

you have psoriasis that covers a large area of the body

if you are allergic to ingredients in this product

When using this product

avoid contact with eyes

If contact occurs, rinse eyes thoroughly with water

Keep out of reach of children.

if swallowed, get medical help or contact a Poison Control Center (1-800-222-1222) right away.

Directions

for best results use at least twice a week or as directed by a doctor
wet hair thoroughly
massage liberal amount of product into scalp
leave lather on for several minutes
rinse thoroughly and repeat if needed

Other information

store between 20° – 25°C (68° – 77°F)

Inactive ingredients

Ascorbic Acid, Cocamidopropyl Betaine, DL Panthenol USP Powder, Green Tea Extract,
Linolemidopropyl PG-Dimonium Chloride Phosphate, PEG-120 Methyl Glucose Dioleate,
Polyquaternium-7, Propylene Glycol, Puried Water, Sodium C-14-16 Olefin Sulfonate, Tea
Tree Oil, Trolamine, Vitamin E Acetate

Questions or comments?

Call 800-824-4894

label